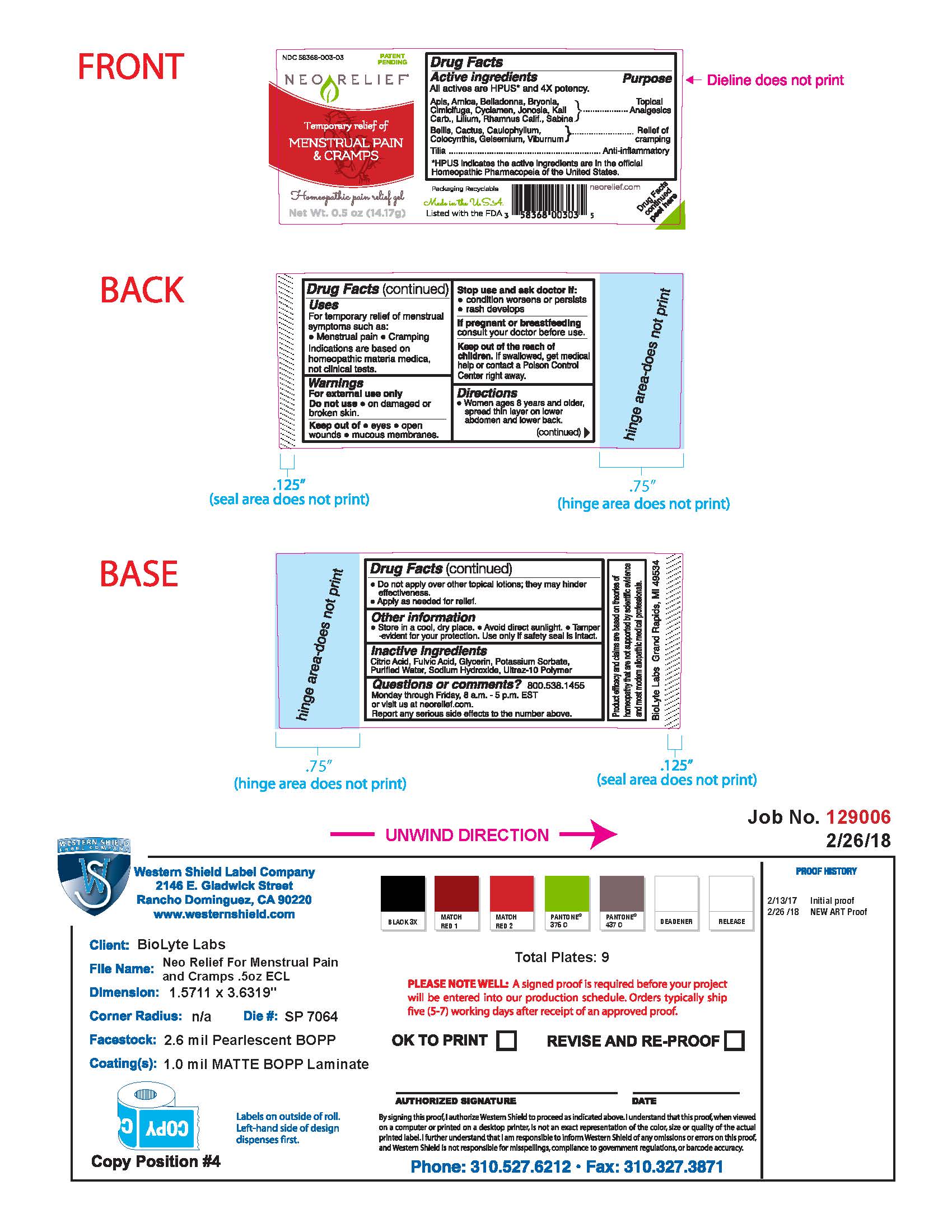 DRUG LABEL: NeoRelief for Menstrual Pain and Cramps
NDC: 58368-003 | Form: GEL
Manufacturer: BioLyte Laboratories, LLC
Category: homeopathic | Type: HUMAN OTC DRUG LABEL
Date: 20260127

ACTIVE INGREDIENTS: POTASSIUM CARBONATE 4 [hp_X]/1 g; FRANGULA CALIFORNICA BARK 4 [hp_X]/1 g; ARNICA MONTANA 4 [hp_X]/1 g; ATROPA BELLADONNA 4 [hp_X]/1 g; BRYONIA ALBA ROOT 4 [hp_X]/1 g; BLACK COHOSH 4 [hp_X]/1 g; CYCLAMEN PURPURASCENS TUBER 4 [hp_X]/1 g; SARACA INDICA BARK 4 [hp_X]/1 g; LILIUM LANCIFOLIUM WHOLE FLOWERING 4 [hp_X]/1 g; JUNIPERUS SABINA LEAFY TWIG 4 [hp_X]/1 g; BELLIS PERENNIS 4 [hp_X]/1 g; SELENICEREUS GRANDIFLORUS STEM 4 [hp_X]/1 g; CAULOPHYLLUM THALICTROIDES ROOT 4 [hp_X]/1 g; CITRULLUS COLOCYNTHIS FRUIT PULP 4 [hp_X]/1 g; GELSEMIUM SEMPERVIRENS ROOT 4 [hp_X]/1 g; VIBURNUM OPULUS BARK 4 [hp_X]/1 g; TILIA X EUROPAEA FLOWER 4 [hp_X]/1 g; APIS MELLIFERA 4 [hp_X]/1 g
INACTIVE INGREDIENTS: POTASSIUM SORBATE; SODIUM HYDROXIDE; CARBOMER HOMOPOLYMER TYPE C (ALLYL PENTAERYTHRITOL CROSSLINKED); FULVIC ACID; GLYCERIN; WATER; CITRIC ACID MONOHYDRATE

Drug Facts Active Ingredients

All actives are HPUS* and 4X potency.

Apis, Arnica, Belladonna, Bryonia, Cimicifuga, Cyclamen, Joneosia, Kali Carb., Lilium, Rhamnus Calif., Sabina

Bellis, Cactus, Caulophyllum, Colocynthis, Gelsemium, Viburnum

Tilia

*HPUS indicates the active ingredients are inthe official Homeopathic Pharmacopeia of the United States.

Purpose

Topical Analgesics

Relief of Cramping

Anti-inflammatory

Uses

For temporary relief of menstrual symptoms such as:

Menstrual pain, Cramping

Indications are based on homeopathic materia medica, not clinical tests.

Warnings

For external use only

Do not use on damged or broken skin.

Keep out of eyes, open wounds, mucous membranes

Warnings

Stop use and ask doctor if:

Condition worsens or persists,

rash develops

Warnings

If pregnant or breastfeeding consult your doctor before use.

Warnings

Keep out of the reach of children. If swallowed, get medical help or contact a Poison Control Center right away.

Directions

Women ages 8 years and older, spread thin layer on lower abdomen and lower back.

Do not apply over other topical lotions; they may hinder effectiveness.

Apply as needed for relief.

Other Information

Store in a cool, dry place. Avoid direct sunlight. Tamper-evident for your protection. Use only if safety seal is intact.

Inactive Ingredients

Citric Acid, Fulvic Acid, Glycerin, Potassium Sorbate, Purified Water, Sodium Hydroxide, Ultrez-10 Polymer.

Questions or Comments?

800.538.1455

Monday through Friday, 8 a.m. - 5 p.m. EST or visit us at neorelief.com.

Reporty any serious side effects to the number above.

Addtional Label Content

Packaging Recyclable

Made in the USA

Listed with the FDA

neorelief.com

Drug Facts continued peel here

FTC required disclosure: Product efficacy and claims are based on theories of homeopathy that re not supported by scientific evidence and most modern allopathic medical professionals.

BioLyte Labs Grand Rapids, MI 49534

NEORELIEF for Menstrual Pain and Cramps

NDC 58368-003-03 Patent Pending

Neo Relief

Temporary relief of

Menstrual pain & cramps

Homeopathic pain relief gel

Net Wt. 0.5 oz (14.17g)